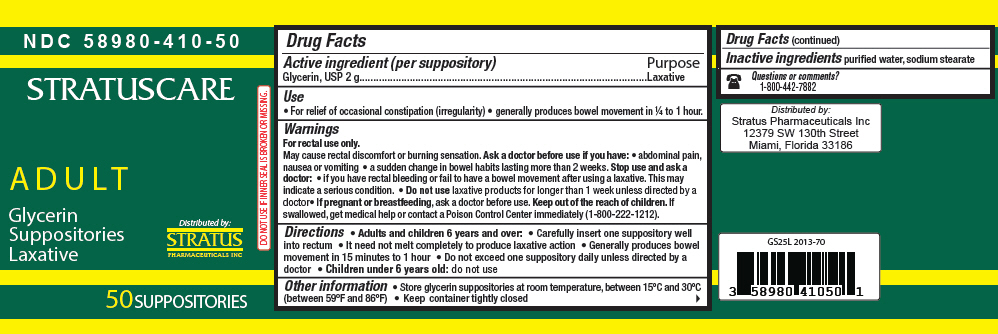 DRUG LABEL: Stratuscare Adult Glycerin
NDC: 58980-410 | Form: SUPPOSITORY
Manufacturer: Stratus Pharmaceuticals
Category: otc | Type: HUMAN OTC DRUG LABEL
Date: 20241104

ACTIVE INGREDIENTS: Glycerin 2 g/1 1
INACTIVE INGREDIENTS: Water; SODIUM STEARATE

Stratuscare Adult Glycerin Suppositories

Drug Facts

Active ingredient (per suppository)

Glycerin, USP 2 g

Purpose

Laxative

Use

- For relief of occasional constipation (irregularity)
- generally produces bowel movement in ¼ to 1 hour.

Warnings

For rectal use only.

May cause rectal discomfort or burning sensation.

Ask a doctor before use if you have:

- abdominal pain, nausea or vomiting
- a sudden change in bowel habits lasting more than 2 weeks.

Stop use and ask a doctor:

- if you have rectal bleeding or fail to have a bowel movement after using a laxative. This may indicate a serious condition.

- Do not use laxative products for longer than 1 week unless directed by a doctor

PREGNANCY OR BREAST FEEDING

- If pregnant or breastfeeding, ask a doctor before use.

KEEP OUT OF REACH OF CHILDREN

Keep out of the reach of children. If swallowed, get medical help or contact a Poison Control Center immediately (1-800-222-1212).

Directions

- Adults and children 6 years and over:
  - Carefully insert one suppository well into rectum
  - It need not melt completely to produce laxative action
  - Generally produces bowel movement in 15 minutes to 1 hour
  - Do not exceed one suppository daily unless directed by a doctor
- Children under 6 years old: do not use

Other information

- Store glycerin suppositories at room temperature, between 15°C and 30°C (between 59°F and 86°F)
- Keep container tightly closed

Inactive ingredients

purified water, sodium stearate

Questions or comments?

1-800-442-7882

Distributed by:
Stratus Pharmaceuticals Inc
12379 SW 130th Street
Miami, Florida 33186

PRINCIPAL DISPLAY PANEL - 50 Suppository Jar Label

NDC 58980-410-50

STRATUSCARE

ADULT

Glycerin
Suppositories
Laxative

Distributed by:
STRATUS
PHARMACEUTICALS INC

DO NOT USE IF INNER SEAL IS BROKEN OR MISSING.

50 SUPPOSITORIES